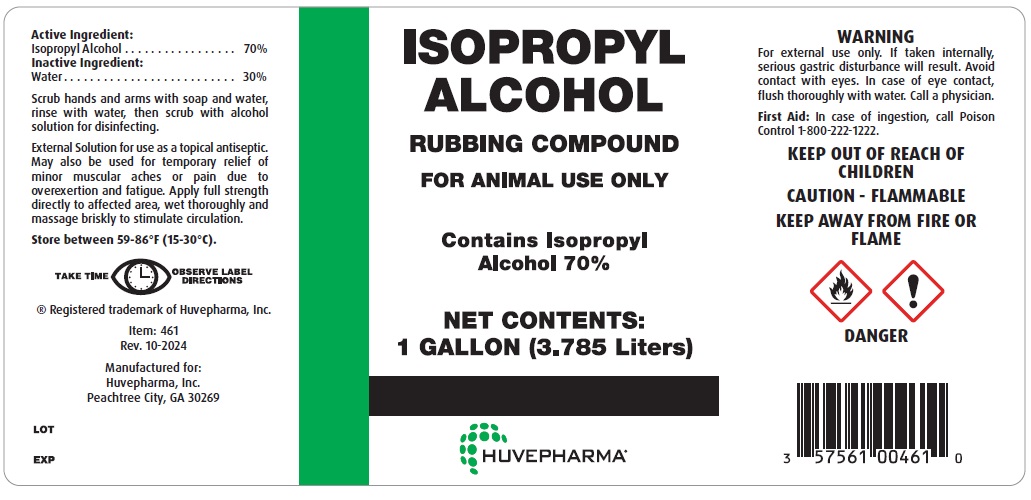 DRUG LABEL: ISOPROPYL ALCOHOL
NDC: 23243-0328 | Form: LIQUID
Manufacturer: Huvepharma, Inc
Category: animal | Type: OTC ANIMAL DRUG LABEL
Date: 20250701

ACTIVE INGREDIENTS: ISOPROPYL ALCOHOL 70 L/100 L
INACTIVE INGREDIENTS: WATER 30 L/100 L

WARNINGS AND PRECAUTIONS

ISOPROPYL ALCOHOL

RUBBING COMPOUND

FOR ANIMAL USE ONLY

Contains Isopropyl Alcohol 70%

Active Ingredients:

Isopropyl Alcohol ................. 70%

Inactive Ingredients:

Water .................................30%

Scrub hands and arms with soap and water, rinse with water, then scrub with alcohol solution for disinfecting.

External Solution for use as a topical antiseptic. May also be used for temporary relief of minor muscular aches or pain due to overexertion and fatigue. Apply full strength directly to affected area, wet thoroughly and massage briskly to stimulate circulation.

Store Between 59-86°F (15-30°C).

WARNING: For external use only. If taken internally, serious gastric disturbance will result. Avoid contact with eyes. In case of eye contact, flush thoroughly with water. Call a physician.

First Aid: In case of ingestion, call Poison Control 1-800-222-1222.

KEEP OUT OF REACH OF CHILDREN

CAUTION - FLAMMABLE

KEEP AWAY FROM FIRE OR FLAME

Manufactured for:

Huvepharma, Inc.

Peachtree City, GA 30269